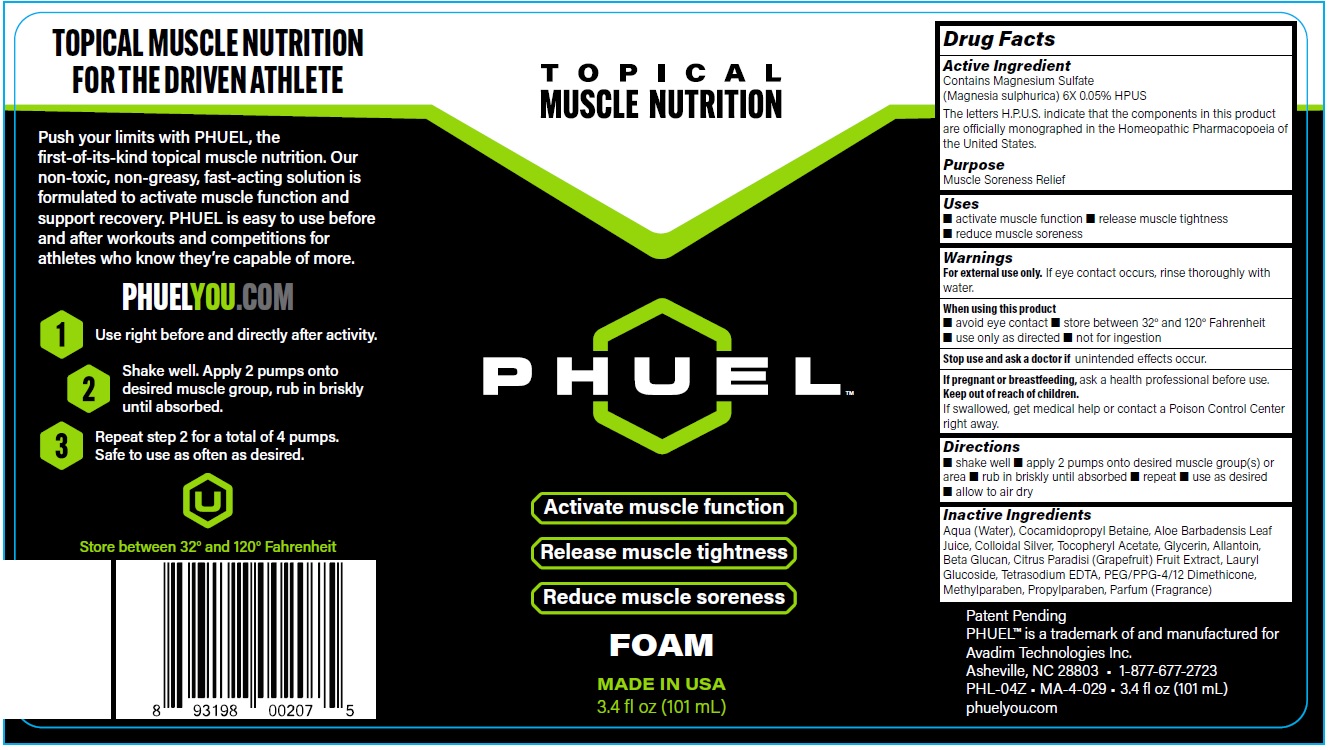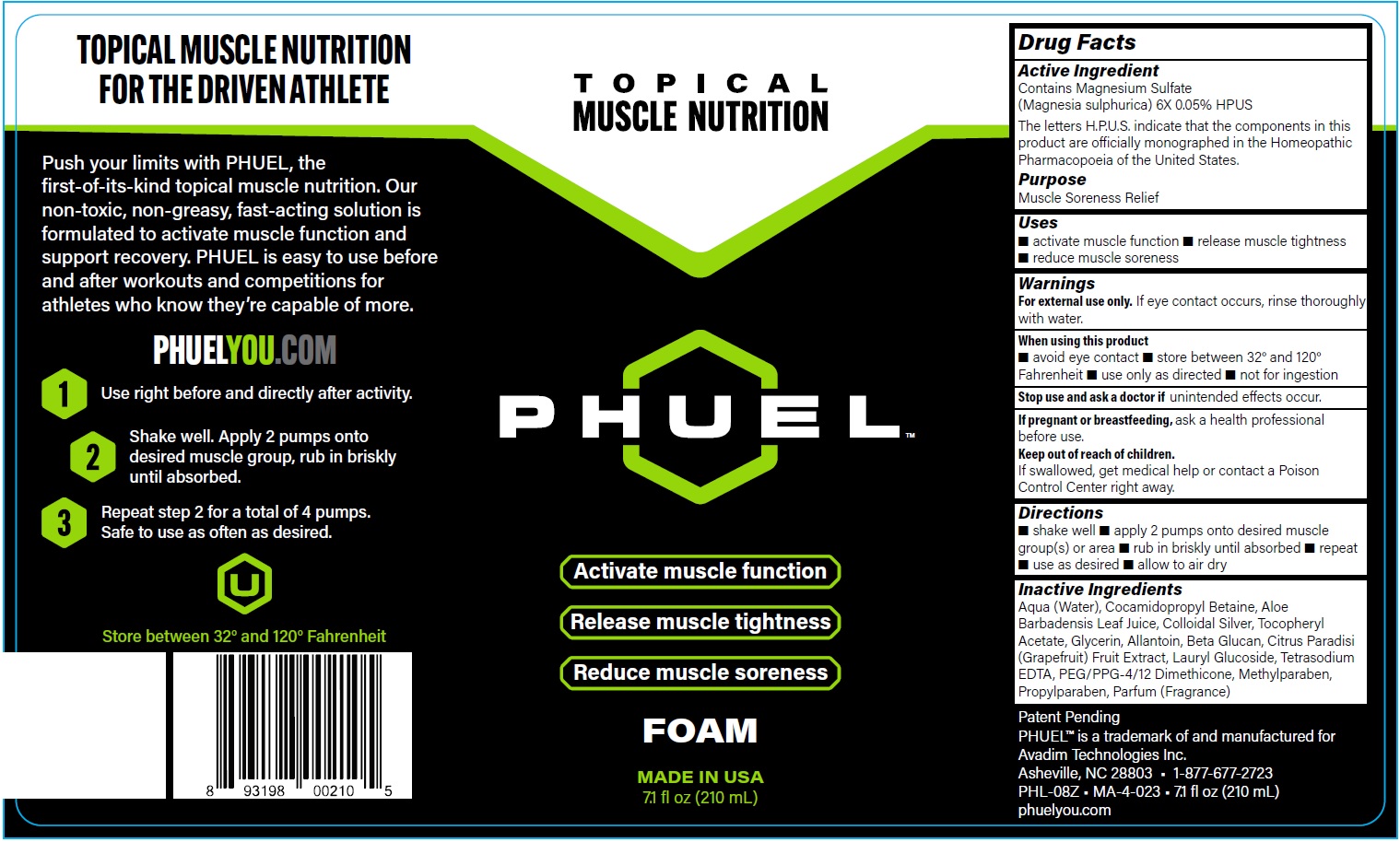 DRUG LABEL: PHUEL
NDC: 61594-010 | Form: SOLUTION
Manufacturer: AVADIM HOLDINGS, INC.
Category: homeopathic | Type: HUMAN OTC DRUG LABEL
Date: 20230425

ACTIVE INGREDIENTS: MAGNESIUM SULFATE HEPTAHYDRATE 6 [hp_X]/1 mL
INACTIVE INGREDIENTS: WATER; COCAMIDOPROPYL BETAINE; ALOE VERA LEAF; SILVER; GLYCERIN; ALLANTOIN; GRAPEFRUIT; LAURYL GLUCOSIDE; EDETATE SODIUM; PEG/PPG-4/12 DIMETHICONE; METHYLPARABEN; PROPYLPARABEN

PHUEL FOAM

Active Ingredient

Contains Magnesium Sulfate (Magnesia sulphurica 6X 0.05% HPUS

The letters H.P.U,S, indicate that the components in this product are officially monographed in the Homeopathic Pharmacopoeia of the United States.

Purpose

Muscle Soreness Relief

Uses

- activate muscle function
- release muscle tightness
- reduce muscle soreness

Warnings

For external use only. If eye contact occurs, rinse thoroughly with water.

When using this product

- avoid eye contact
- store between 32° and 120° Fahrenheit
- use only as directed
- not for ingestion

Stop use and ask a doctor if

unintended effects occur.

If pregnant or breastfeeding,

ask a health professional before use.

Keep out of reach of children.

If swallowed, get medical help or contact a Poison Control Center right away.

Directions

- shake well
- apply 2 pumps onto desired muscle group(s) or area
- rub in briskly until absorbed
- repeat
- use as desired
- allow to air dry

Inactive Ingredients

Aqua (Water), Cocamidopropyl Betaine, Aloe Barbadensis Leaf Juice, Colloidal Silver, Tocopheryl Acetate, Glycerin, Allantoin, Beta Glucan, Citrus Paradisi (Grapefruit) Fruit Extract, Lauryl Glucoside, Tetrasodium EDTA, PEG/PPG-4/12 Dimethicone, Methylparaben, Propylparaben, Parfum (Fragrance)